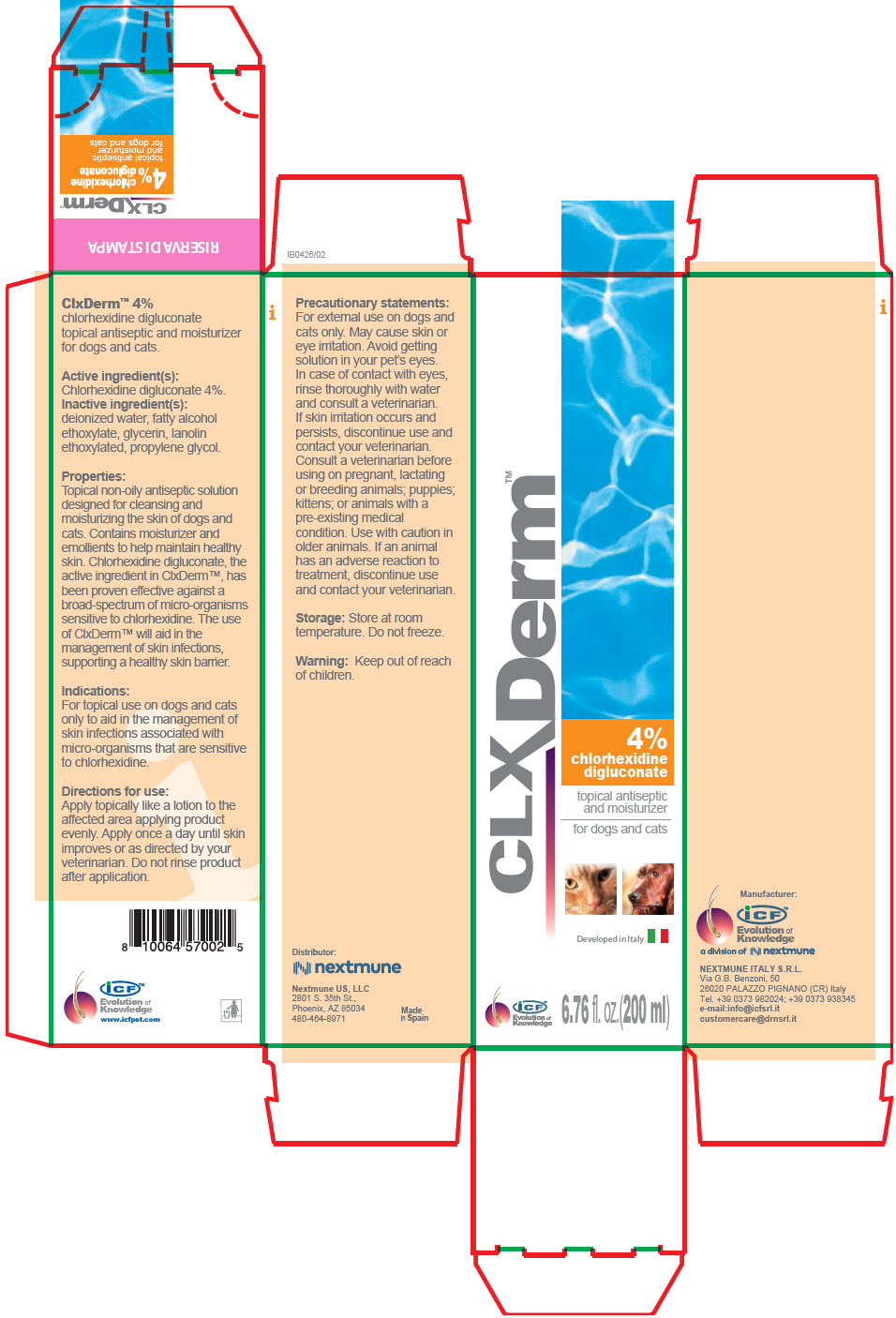 DRUG LABEL: Clx Derm chlorhexidine digluconate antiseptic and moisturizer for dogs and cats
NDC: 86127-003 | Form: SOLUTION
Manufacturer: Nextmune AB
Category: animal | Type: OTC ANIMAL DRUG LABEL
Date: 20220111

ACTIVE INGREDIENTS: CHLORHEXIDINE GLUCONATE 40 mg/1 mL
INACTIVE INGREDIENTS: water; glycerin; propylene glycol; PEG-75 Lanolin; ISOTRIDECYL ALCOHOL

ClxDerm™ 4%

VETERINARY INDICATIONS

chlorhexidine digluconate topical antiseptic and moisturizer for dogs and cats.

Active ingredient(s):

Chlorhexidine digluconate 4%.

Inactive ingredient(s):

deionized water, fatty alcohol ethoxylate, glycerin, lanolin ethoxylated, propylene glycol.

Properties:

Topical non-oily antiseptic solution designed for cleansing and moisturizing the skin of dogs and cats. Contains moisturizer and emollients to help maintain healthy skin. Chlorhexidine digluconate, the active ingredient in ClxDerm™, has been proven effective against a broad-spectrum of micro-organisms sensitive to chlorhexidine. The use of ClxDerm™ will aid in the management of skin infections, supporting a healthy skin barrier.

Indications:

For topical use on dogs and cats only to aid in the management of skin infections associated with micro-organisms that are sensitive to chlorhexidine.

Directions for use:

Apply topically like a lotion to the affected area applying product evenly. Apply once a day until skin improves or as directed by your veterinarian. Do not rinse product after application.

Precautionary statements:

For external use on dogs and cats only. May cause skin or eye irritation. Avoid getting solution in your pet's eyes. In case of contact with eyes, rinse thoroughly with water and consult a veterinarian. If skin irritation occurs and persists, discontinue use and contact your veterinarian. Consult a veterinarian before using on pregnant, lactating or breeding animals; puppies; kittens; or animals with a pre-existing medical condition. Use with caution in older animals. If an animal has an adverse reaction to treatment, discontinue use and contact your veterinarian.

Storage: Store at room temperature. Do not freeze.

WARNINGS

Warning: Keep out of reach of children.

iCF™
Evolution of
Knowledge
www.icfpet.com

Distributor:
Nextmune US, LLC
2801 S. 35th St.,
Phoenix, AZ 85034
480-464-8971

Made
in Spain

Manufacturer:

iCF™
Evolution of
Knowledge

a division of

NEXTMUNE ITALY S.R.L.
Via G.B. Benzoni, 50
26020 PALAZZO PIGNANO (CR) Italy
Tel. +39 0373 982024; +39 0373 938345
e-mail:info@icfsrl.it
customercare@drnsrl.it

PRINCIPAL DISPLAY PANEL - 200 ml Bottle Carton

CLXDerm™
4%
chlorhexidine
digluconate

topical antiseptic
and moisturizer

for dogs and cats

Developed in Italy

iCF™
Evolution of
Knowledge

6.76 fl. oz.(200 ml)